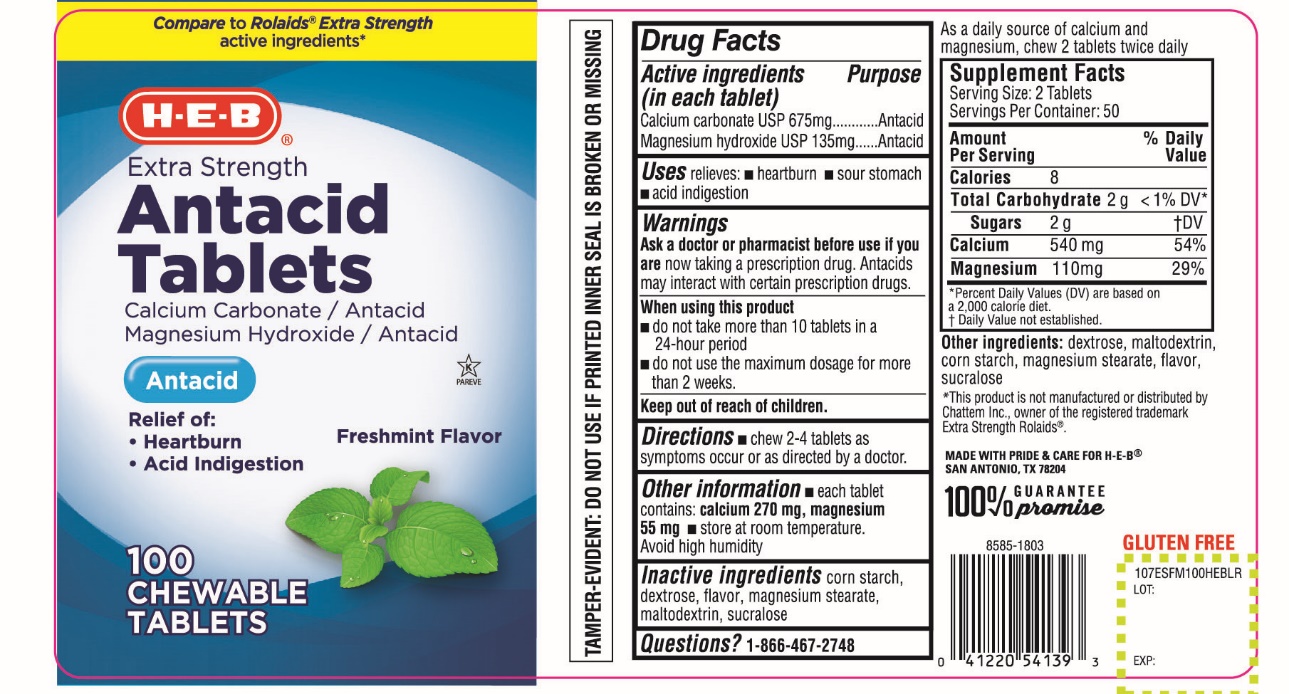 DRUG LABEL: HEB Extra Strength
NDC: 37808-207 | Form: TABLET, CHEWABLE
Manufacturer: HEB
Category: otc | Type: HUMAN OTC DRUG LABEL
Date: 20211118

ACTIVE INGREDIENTS: CALCIUM CARBONATE 675 mg/1 1; MAGNESIUM HYDROXIDE 135 mg/1 1
INACTIVE INGREDIENTS: STARCH, CORN; DEXTROSE, UNSPECIFIED FORM; MAGNESIUM STEARATE; MALTODEXTRIN; SUCRALOSE

HEB Extra Strength Antacid Tablets Freshmint Flavor

Drug Facts

Active ingredients (in each tablet)

Calcium Carbonate USP 675 mg
Magnesium hydroxide USP 135 mg

Purpose

Antacid

Antacid

Uses

relieves:

- heartburn
- sour stomach
- acid indigestion

Warnings

Ask a doctor or pharmacist before use if you are

now taking a prescription drug. Antacids may interact with certain prescription drugs.

When using this product

- do not take more than 10 tablets in a 24-hour period,
- do not use the maximum dosage for more than 2 weeks

Directions

- chew 2-4 tablets as symptoms occur or as directed by a doctor.

Other information

- each tablet contains: calcium 270 mg, magnesium 55 mg
- store at room temperature

Avoid high humidity.

As a daily source of calcium and magnesium, chew 2 tablets twice daily

Supplement Facts

Serving Size: 2 Tablets

Servings Per Container: 50

Amount Per Serving | % Daily Value
Calories 8
Total Carbohydrate 2 g | <1% DV*
Sugars 2g | †DV
Calcium 540 mg | 54%
Magnesium 110 mg | 29%

*Percent Daily Values (DV) are based on a 2,000 calories diet.

†Daily Value not established.

Inactive ingredients

dextrose, maltodextrin, corn starch, magnesium stearate, flavor, sucralose.

Questions?

1-866-467-2748

PRINCIPAL DISPLAY PANEL

H-E-B®

NDC# 37808-207-10

Compare to Rolaids® Extra Strength active ingredients*

Extra Strength

Antacid Tablets

Calcium Carbonate/Antacid

Magnesium Hydroxide/Antacid

Antacid

Freshmint Flavor

Relieves:

- Heartburn
- Acid Indigestion

100 CHEWABLE TABLETS

GLUTEN FREE

K PAREVE

100% GURANTEE promise

TAMPER EVIDENT: DO NOT USE IF PRINTED INNER SEAL IS BROKEN OR MISSING

*This product is not manufactured or distributed by Chattem Inc., owner of the registered trademark Extra Strength Rolaids®

MADE WITH PRIDE & CARE FOR H-E-B®

SAN ANTONIA, TX 78204